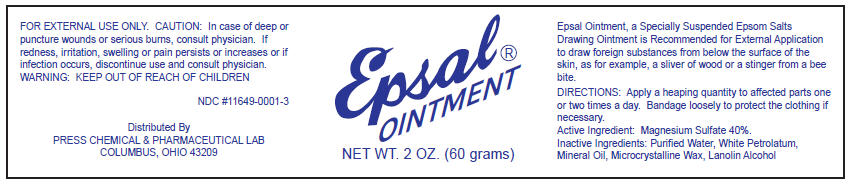 DRUG LABEL: Epsal
NDC: 11649-0001 | Form: OINTMENT
Manufacturer: Press Chemical and Pharmaceutical Laboratories
Category: otc | Type: HUMAN OTC DRUG LABEL
Date: 20200124

ACTIVE INGREDIENTS: Magnesium Sulfate, Unspecified Form 400 mg/1 g
INACTIVE INGREDIENTS: Petrolatum 143 mg/1 g; Mineral Oil; Microcrystalline Wax; Lanolin Alcohols

Epsal Ointment

INDICATIONS AND USAGE

PURPOSE

Epsal Ointment, a Specially Suspended Epsom Salts Drawing Ointment is Recommended for External Application to draw foreign substances from below the surface of the skin, as for example, a sliver of wood or a stinger from a bee bite.

DIRECTIONS

Apply a heaping quantity to affected parts one or two times a day. Bandage loosely to protect the clothing if necessary.

Active Ingredient

Magnesium Sulfate 40%.

Inactive Ingredients

Purified Water, White Petrolatum, Mineral Oil, Microcrystalline Wax, Lanolin Alcohol

WARNINGS

FOR EXTERNAL USE ONLY. CAUTION: In case of deep or puncture wounds or serious burns, consult physician. If redness, irritation, swelling or pain persists or increases or if infection occurs, discontinue use and consult physician.

WARNING

KEEP OUT OF REACH OF CHILDREN

NDC #11649-0001-3

Distributed By
PRESS CHEMICAL & PHARMACEUTICAL LAB
COLUMBUS, OHIO 43209

PRINCIPAL DISPLAY PANEL - 60 gram Jar Label

Epsal®
OINTMENT

NET WT. 2 OZ. (60 grams)